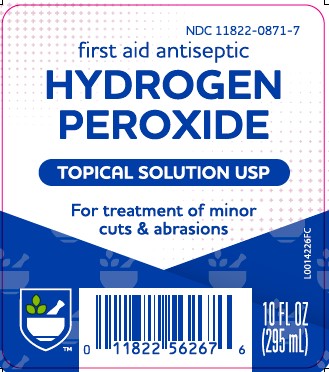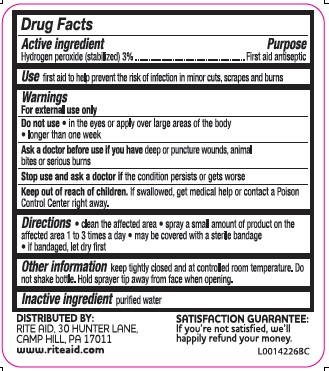 DRUG LABEL: Hydrogen Peroxide
NDC: 11822-0871 | Form: SOLUTION
Manufacturer: Rite Aid Corporation
Category: otc | Type: HUMAN OTC DRUG LABEL
Date: 20260130

ACTIVE INGREDIENTS: HYDROGEN PEROXIDE 0.3 kg/100 L
INACTIVE INGREDIENTS: WATER

Rite Aid 871.001/871AA
Hydrogen Peroxide

Active ingredient

Hydrogen peroxide (stabilized) 3%

Purpose

First aid antiseptic

Use

• first aid to help prevent the risk of infection in minor cuts, scrapes and burns

Warnings

for external use only

Do not use

- in the eyes or apply over large areas of the body
- longer than one week

Ask a doctor before use if you have

deep or puncture wounds, animal bites or serious burns

Stop use and ask a doctor if

the condition persists or gets worse

Keep out of reach of children.

If swallowed, get medical help or contact a Poison Control Center right away.

Directions

- clean the affected area
- spray a small amount of product on the affected area 1 to 3 times a day
- may be covered with a sterile bandage
- if bandaged, let dry first

Other information

keep tightly closed and at controlled room temperature. Do not shake bottle. Hold sprayer tip away from face when opening.

Inactive ingredient

purified water

ADVERSE REACTION

DISTRIBUTED BY: RITE AID

30 HUNTER LANE, CAMP HILL PA 17011

www.riteaid.com

SATISFACTION GUARANTEE: If you're not satisfied, we'll happily refund your money.

principal display panel

NDC 11822-0871-7

first aid antiseptic

hydrogen peroxide

topical solution USP

For treatment of minor cuts & abrasions

10 FL OZ (295 mL)